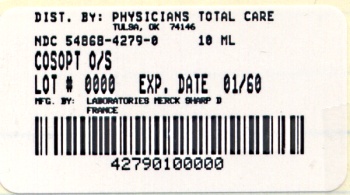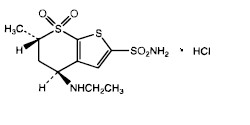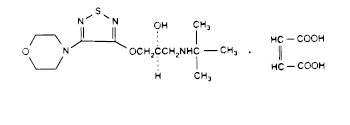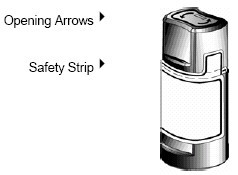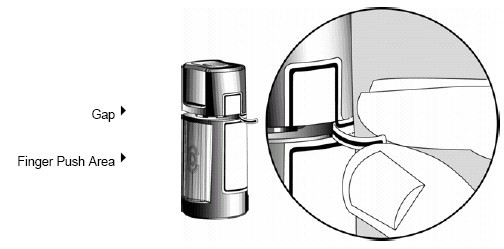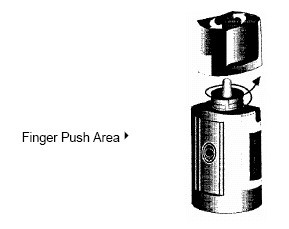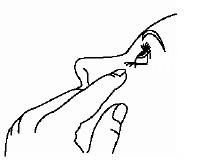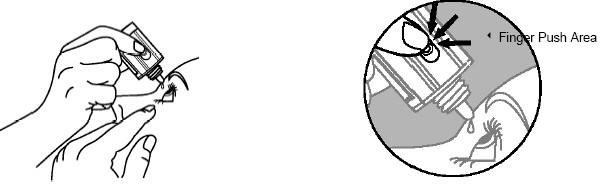 DRUG LABEL: Cosopt
NDC: 54868-4279 | Form: SOLUTION
Manufacturer: Physicians Total Care, Inc.
Category: prescription | Type: HUMAN PRESCRIPTION DRUG LABEL
Date: 20100505

ACTIVE INGREDIENTS: DORZOLAMIDE HYDROCHLORIDE 20 mg/1 mL; TIMOLOL MALEATE 5 mg/1 mL
INACTIVE INGREDIENTS: BENZALKONIUM CHLORIDE; HYDROXYETHYL CELLULOSE (2000 CPS AT 1%); MANNITOL; TRISODIUM CITRATE DIHYDRATE; SODIUM HYDROXIDE; WATER

COSOPT®
(dorzolamide hydrochloride-timolol maleate ophthalmic solution)
Sterile Ophthalmic Solution

DESCRIPTION

COSOPT (dorzolamide hydrochloride-timolol maleate ophthalmic solution) is the combination of a topical carbonic anhydrase inhibitor and a topical beta-adrenergic receptor blocking agent.

Dorzolamide hydrochloride is described chemically as: (4S-trans)-4-(ethylamino)-5,6-dihydro-6-methyl-4H-thieno[2,3-b]thiopyran-2-sulfonamide 7,7-dioxide monohydrochloride. Dorzolamide hydrochloride is optically active. The specific rotation is:

[α] 25°C (C=1, water) = ~ -17°.

405 nm

Its empirical formula is C10H16N2O4S3•HCl and its structural formula is:

Dorzolamide hydrochloride has a molecular weight of 360.91. It is a white to off-white, crystalline powder, which is soluble in water and slightly soluble in methanol and ethanol.

Timolol maleate is described chemically as: (-)-1-(tert-butylamino)-3-[(4-morpholino-1,2,5-thiadiazol-3-yl)oxy]-2-propanol maleate (1:1) (salt). Timolol maleate possesses an asymmetric carbon atom in its structure and is provided as the levo-isomer. The optical rotation of timolol maleate is:

[α] 25°C in 1N HCl (C=5) = -12.2° (-11.7° to -12.5°).

405 nm

Its molecular formula is C13H24N4O3S•C4H4O4 and its structural formula is:

Timolol maleate has a molecular weight of 432.50. It is a white, odorless, crystalline powder which is soluble in water, methanol, and alcohol. Timolol maleate is stable at room temperature.

COSOPT is supplied as a sterile, isotonic, buffered, slightly viscous, aqueous solution. The pH of the solution is approximately 5.65, and the osmolarity is 242-323 mOsM. Each mL of COSOPT contains 20 mg dorzolamide (22.26 mg of dorzolamide hydrochloride) and 5 mg timolol (6.83 mg timolol maleate). Inactive ingredients are sodium citrate, hydroxyethyl cellulose, sodium hydroxide, mannitol, and water for injection. Benzalkonium chloride 0.0075% is added as a preservative.

CLINICAL PHARMACOLOGY

Mechanism of Action

COSOPT is comprised of two components: dorzolamide hydrochloride and timolol maleate. Each of these two components decreases elevated intraocular pressure, whether or not associated with glaucoma, by reducing aqueous humor secretion. Elevated intraocular pressure is a major risk factor in the pathogenesis of optic nerve damage and glaucomatous visual field loss. The higher the level of intraocular pressure, the greater the likelihood of glaucomatous field loss and optic nerve damage.

Dorzolamide hydrochloride is an inhibitor of human carbonic anhydrase II. Inhibition of carbonic anhydrase in the ciliary processes of the eye decreases aqueous humor secretion, presumably by slowing the formation of bicarbonate ions with subsequent reduction in sodium and fluid transport. Timolol maleate is a beta1 and beta2 (non-selective) adrenergic receptor blocking agent that does not have significant intrinsic sympathomimetic, direct myocardial depressant, or local anesthetic (membrane-stabilizing) activity. The combined effect of these two agents administered as COSOPT b.i.d. results in additional intraocular pressure reduction compared to either component administered alone, but the reduction is not as much as when dorzolamide t.i.d. and timolol b.i.d. are administered concomitantly (see Clinical Studies).

Pharmacokinetics/Pharmacodynamics

Dorzolamide Hydrochloride

When topically applied, dorzolamide reaches the systemic circulation. To assess the potential for systemic carbonic anhydrase inhibition following topical administration, drug and metabolite concentrations in RBCs and plasma and carbonic anhydrase inhibition in RBCs were measured. Dorzolamide accumulates in RBCs during chronic dosing as a result of binding to CA-II. The parent drug forms a single N-desethyl metabolite, which inhibits CA-II less potently than the parent drug but also inhibits CA-I. The metabolite also accumulates in RBCs where it binds primarily to CA-I. Plasma concentrations of dorzolamide and metabolite are generally below the assay limit of quantitation (15nM). Dorzolamide binds moderately to plasma proteins (approximately 33%).

Dorzolamide is primarily excreted unchanged in the urine; the metabolite also is excreted in urine. After dosing is stopped, dorzolamide washes out of RBCs nonlinearly, resulting in a rapid decline of drug concentration initially, followed by a slower elimination phase with a half-life of about four months.

To simulate the systemic exposure after long-term topical ocular administration, dorzolamide was given orally to eight healthy subjects for up to 20 weeks. The oral dose of 2 mg b.i.d. closely approximates the amount of drug delivered by topical ocular administration of dorzolamide 2% t.i.d. Steady state was reached within 8 weeks. The inhibition of CA-II and total carbonic anhydrase activities was below the degree of inhibition anticipated to be necessary for a pharmacological effect on renal function and respiration in healthy individuals.

Timolol Maleate

In a study of plasma drug concentrations in six subjects, the systemic exposure to timolol was determined following twice daily topical administration of timolol maleate ophthalmic solution 0.5%. The mean peak plasma concentration following morning dosing was 0.46 ng/mL.

Clinical Studies

Clinical studies of 3 to 15 months duration were conducted to compare the IOP-lowering effect over the course of the day of COSOPT b.i.d. (dosed morning and bedtime) to individually- and concomitantly-administered 0.5% timolol (b.i.d.) and 2.0% dorzolamide (b.i.d. and t.i.d.). The IOP-lowering effect of COSOPT b.i.d. was greater (1-3 mmHg) than that of monotherapy with either 2.0% dorzolamide t.i.d. or 0.5% timolol b.i.d. The IOP-lowering effect of COSOPT b.i.d. was approximately 1 mmHg less than that of concomitant therapy with 2.0% dorzolamide t.i.d. and 0.5% timolol b.i.d.

Open-label extensions of two studies were conducted for up to 12 months. During this period, the IOP-lowering effect of COSOPT b.i.d. was consistent during the 12 month follow-up period.

INDICATIONS AND USAGE

COSOPT is indicated for the reduction of elevated intraocular pressure in patients with open-angle glaucoma or ocular hypertension who are insufficiently responsive to beta-blockers (failed to achieve target IOP determined after multiple measurements over time). The IOP-lowering of COSOPT b.i.d. was slightly less than that seen with the concomitant administration of 0.5% timolol b.i.d. and 2.0% dorzolamide t.i.d. (see CLINICAL PHARMACOLOGY, Clinical Studies).

CONTRAINDICATIONS

COSOPT is contraindicated in patients with (1) bronchial asthma; (2) a history of bronchial asthma; (3) severe chronic obstructive pulmonary disease (see WARNINGS); (4) sinus bradycardia; (5) second or third degree atrioventricular block; (6) overt cardiac failure (see WARNINGS); (7) cardiogenic shock; or (8) hypersensitivity to any component of this product.

WARNINGS

Systemic Exposure

COSOPT contains dorzolamide, a sulfonamide, and timolol maleate, a beta-adrenergic blocking agent; and although administered topically, is absorbed systemically. Therefore, the same types of adverse reactions that are attributable to sulfonamides and/or systemic administration of beta-adrenergic blocking agents may occur with topical administration. For example, severe respiratory reactions and cardiac reactions, including death due to bronchospasm in patients with asthma, and rarely death in association with cardiac failure, have been reported following systemic or ophthalmic administration of timolol maleate (see CONTRAINDICATIONS). Fatalities have occurred, although rarely, due to severe reactions to sulfonamides including Stevens-Johnson syndrome, toxic epidermal necrolysis, fulminant hepatic necrosis, agranulocytosis, aplastic anemia, and other blood dyscrasias. Sensitization may recur when a sulfonamide is readministered irrespective of the route of administration. If signs of serious reactions or hypersensitivity occur, discontinue the use of this preparation.

Cardiac Failure

Sympathetic stimulation may be essential for support of the circulation in individuals with diminished myocardial contractility, and its inhibition by beta-adrenergic receptor blockade may precipitate more severe failure.

In Patients Without a History of Cardiac Failure continued depression of the myocardium with beta-blocking agents over a period of time can, in some cases, lead to cardiac failure. At the first sign or symptom of cardiac failure, COSOPT should be discontinued.

Obstructive Pulmonary Disease

Patients with chronic obstructive pulmonary disease (e.g., chronic bronchitis, emphysema) of mild or moderate severity, bronchospastic disease, or a history of bronchospastic disease (other than bronchial asthma or a history of bronchial asthma, in which COSOPT is contraindicated [see CONTRAINDICATIONS]) should, in general, not receive beta-blocking agents, including COSOPT.

Major Surgery

The necessity or desirability of withdrawal of beta-adrenergic blocking agents prior to major surgery is controversial. Beta-adrenergic receptor blockade impairs the ability of the heart to respond to beta-adrenergically mediated reflex stimuli. This may augment the risk of general anesthesia in surgical procedures. Some patients receiving beta-adrenergic receptor blocking agents have experienced protracted severe hypotension during anesthesia. Difficulty in restarting and maintaining the heartbeat has also been reported. For these reasons, in patients undergoing elective surgery, some authorities recommend gradual withdrawal of beta-adrenergic receptor blocking agents.

If necessary during surgery, the effects of beta-adrenergic blocking agents may be reversed by sufficient doses of adrenergic agonists.

Diabetes Mellitus

Beta-adrenergic blocking agents should be administered with caution in patients subject to spontaneous hypoglycemia or to diabetic patients (especially those with labile diabetes) who are receiving insulin or oral hypoglycemic agents. Beta-adrenergic receptor blocking agents may mask the signs and symptoms of acute hypoglycemia.

Thyrotoxicosis

Beta-adrenergic blocking agents may mask certain clinical signs (e.g., tachycardia) of hyperthyroidism. Patients suspected of developing thyrotoxicosis should be managed carefully to avoid abrupt withdrawal of beta-adrenergic blocking agents that might precipitate a thyroid storm.

PRECAUTIONS

General

Dorzolamide has not been studied in patients with severe renal impairment (CrCl <30 mL/min). Because dorzolamide and its metabolite are excreted predominantly by the kidney, COSOPT is not recommended in such patients.

Dorzolamide has not been studied in patients with hepatic impairment and should therefore be used with caution in such patients.

While taking beta-blockers, patients with a history of atopy or a history of severe anaphylactic reactions to a variety of allergens may be more reactive to repeated accidental, diagnostic, or therapeutic challenge with such allergens. Such patients may be unresponsive to the usual doses of epinephrine used to treat anaphylactic reactions.

In clinical studies, local ocular adverse effects, primarily conjunctivitis and lid reactions, were reported with chronic administration of COSOPT. Many of these reactions had the clinical appearance and course of an allergic-type reaction that resolved upon discontinuation of drug therapy. If such reactions are observed, COSOPT should be discontinued and the patient evaluated before considering restarting the drug. (See ADVERSE REACTIONS.)

The management of patients with acute angle-closure glaucoma requires therapeutic interventions in addition to ocular hypotensive agents. COSOPT has not been studied in patients with acute angle-closure glaucoma.

Choroidal detachment after filtration procedures has been reported with the administration of aqueous suppressant therapy (e.g., timolol).

Beta-adrenergic blockade has been reported to potentiate muscle weakness consistent with certain myasthenic symptoms (e.g., diplopia, ptosis, and generalized weakness). Timolol has been reported rarely to increase muscle weakness in some patients with myasthenia gravis or myasthenic symptoms.

There have been reports of bacterial keratitis associated with the use of multiple-dose containers of topical ophthalmic products. These containers had been inadvertently contaminated by patients who, in most cases, had a concurrent corneal disease or a disruption of the ocular epithelial surface. (See PRECAUTIONS, Information for Patients.)

There is an increased potential for developing corneal edema in patients with low endothelial cell counts. Precautions should be used when prescribing COSOPT to this group of patients.

Information for Patients

Patients with bronchial asthma, a history of bronchial asthma, severe chronic obstructive pulmonary disease, sinus bradycardia, second or third degree atrioventricular block, or cardiac failure should be advised not to take this product. (See CONTRAINDICATIONS.)

COSOPT contains dorzolamide (which is a sulfonamide) and, although administered topically, is absorbed systemically. Therefore the same types of adverse reactions that are attributable to sulfonamides may occur with topical administration, including severe skin reactions. Patients should be advised that if serious or unusual reactions or signs of hypersensitivity occur, they should discontinue the use of the product (see WARNINGS).

Patients should be advised that if they develop any ocular reactions, particularly conjunctivitis and lid reactions, they should discontinue use and seek their physician's advice.

Patients should be instructed to avoid allowing the tip of the dispensing container to contact the eye or surrounding structures.

Patients should also be instructed that ocular solutions, if handled improperly or if the tip of the dispensing container contacts the eye or surrounding structures, can become contaminated by common bacteria known to cause ocular infections. Serious damage to the eye and subsequent loss of vision may result from using contaminated solutions. (See PRECAUTIONS, General.)

Patients also should be advised that if they have ocular surgery or develop an intercurrent ocular condition (e.g., trauma or infection), they should immediately seek their physician's advice concerning the continued use of the present multidose container.

If more than one topical ophthalmic drug is being used, the drugs should be administered at least ten minutes apart.

Patients should be advised that COSOPT contains benzalkonium chloride which may be absorbed by soft contact lenses. Contact lenses should be removed prior to administration of the solution. Lenses may be reinserted 15 minutes following administration of COSOPT.

Drug Interactions

Carbonic anhydrase inhibitors: There is a potential for an additive effect on the known systemic effects of carbonic anhydrase inhibition in patients receiving an oral carbonic anhydrase inhibitor and COSOPT. The concomitant administration of COSOPT and oral carbonic anhydrase inhibitors is not recommended.

Acid-base disturbances: Although acid-base and electrolyte disturbances were not reported in the clinical trials with dorzolamide hydrochloride ophthalmic solution, these disturbances have been reported with oral carbonic anhydrase inhibitors and have, in some instances, resulted in drug interactions (e.g., toxicity associated with high-dose salicylate therapy). Therefore, the potential for such drug interactions should be considered in patients receiving COSOPT.

Beta-adrenergic blocking agents: Patients who are receiving a beta-adrenergic blocking agent orally and COSOPT should be observed for potential additive effects of beta-blockade, both systemic and on intraocular pressure. The concomitant use of two topical beta-adrenergic blocking agents is not recommended.

Calcium antagonists: Caution should be used in the coadministration of beta-adrenergic blocking agents, such as COSOPT, and oral or intravenous calcium antagonists because of possible atrioventricular conduction disturbances, left ventricular failure, and hypotension. In patients with impaired cardiac function, coadministration should be avoided.

Catecholamine-depleting drugs: Close observation of the patient is recommended when a beta-blocker is administered to patients receiving catecholamine-depleting drugs such as reserpine, because of possible additive effects and the production of hypotension and/or marked bradycardia, which may result in vertigo, syncope, or postural hypotension.

Digitalis and calcium antagonists: The concomitant use of beta-adrenergic blocking agents with digitalis and calcium antagonists may have additive effects in prolonging atrioventricular conduction time.

CYP2D6 inhibitors: Potentiated systemic beta-blockade (e.g., decreased heart rate, depression) has been reported during combined treatment with CYP2D6 inhibitors (e.g., quinidine, SSRIs) and timolol.

Clonidine: Oral beta-adrenergic blocking agents may exacerbate the rebound hypertension which can follow the withdrawal of clonidine. There have been no reports of exacerbation of rebound hypertension with ophthalmic timolol maleate.

Injectable Epinephrine: (See PRECAUTIONS, General, Anaphylaxis.)

Carcinogenesis, Mutagenesis, Impairment of Fertility

In a two-year study of dorzolamide hydrochloride administered orally to male and female Sprague-Dawley rats, urinary bladder papillomas were seen in male rats in the highest dosage group of 20 mg/kg/day (250 times the recommended human ophthalmic dose). Papillomas were not seen in rats given oral doses equivalent to approximately 12 times the recommended human ophthalmic dose. No treatment-related tumors were seen in a 21-month study in female and male mice given oral doses up to 75 mg/kg/day (~900 times the recommended human ophthalmic dose).

The increased incidence of urinary bladder papillomas seen in the high-dose male rats is a class-effect of carbonic anhydrase inhibitors in rats. Rats are particularly prone to developing papillomas in response to foreign bodies, compounds causing crystalluria, and diverse sodium salts.

No changes in bladder urothelium were seen in dogs given oral dorzolamide hydrochloride for one year at 2 mg/kg/day (25 times the recommended human ophthalmic dose) or monkeys dosed topically to the eye at 0.4 mg/kg/day (~5 times the recommended human ophthalmic dose) for one year.

In a two-year study of timolol maleate administered orally to rats, there was a statistically significant increase in the incidence of adrenal pheochromocytomas in male rats administered 300 mg/kg/day (approximately 42,000 times the systemic exposure following the maximum recommended human ophthalmic dose). Similar differences were not observed in rats administered oral doses equivalent to approximately 14,000 times the maximum recommended human ophthalmic dose.

In a lifetime oral study of timolol maleate in mice, there were statistically significant increases in the incidence of benign and malignant pulmonary tumors, benign uterine polyps and mammary adenocarcinomas in female mice at 500 mg/kg/day, (approximately 71,000 times the systemic exposure following the maximum recommended human ophthalmic dose), but not at 5 or 50 mg/kg/day (approximately 700 or 7,000, respectively, times the systemic exposure following the maximum recommended human ophthalmic dose). In a subsequent study in female mice, in which post-mortem examinations were limited to the uterus and the lungs, a statistically significant increase in the incidence of pulmonary tumors was again observed at 500 mg/kg/day.

The increased occurrence of mammary adenocarcinomas was associated with elevations in serum prolactin which occurred in female mice administered oral timolol at 500 mg/kg/day, but not at doses of 5 or 50 mg/kg/day. An increased incidence of mammary adenocarcinomas in rodents has been associated with administration of several other therapeutic agents that elevate serum prolactin, but no correlation between serum prolactin levels and mammary tumors has been established in humans. Furthermore, in adult human female subjects who received oral dosages of up to 60 mg of timolol maleate (the maximum recommended human oral dosage), there were no clinically meaningful changes in serum prolactin.

The following tests for mutagenic potential were negative for dorzolamide: (1) in vivo (mouse) cytogenetic assay; (2) in vitro chromosomal aberration assay; (3) alkaline elution assay; (4) V-79 assay; and (5) Ames test.

Timolol maleate was devoid of mutagenic potential when tested in vivo (mouse) in the micronucleus test and cytogenetic assay (doses up to 800 mg/kg) and in vitro in a neoplastic cell transformation assay (up to 100 μg/mL). In Ames tests the highest concentrations of timolol employed, 5,000 or 10,000 μg/plate, were associated with statistically significant elevations of revertants observed with tester strain TA100 (in seven replicate assays), but not in the remaining three strains. In the assays with tester strain TA100, no consistent dose response relationship was observed, and the ratio of test to control revertants did not reach 2. A ratio of 2 is usually considered the criterion for a positive Ames test.

Reproduction and fertility studies in rats with either timolol maleate or dorzolamide hydrochloride demonstrated no adverse effect on male or female fertility at doses up to approximately 100 times the systemic exposure following the maximum recommended human ophthalmic dose.

Pregnancy

Teratogenic Effects

Pregnancy Category C. Developmental toxicity studies with dorzolamide hydrochloride in rabbits at oral doses of ≥2.5 mg/kg/day (31 times the recommended human ophthalmic dose) revealed malformations of the vertebral bodies. These malformations occurred at doses that caused metabolic acidosis with decreased body weight gain in dams and decreased fetal weights. No treatment-related malformations were seen at 1.0 mg/kg/day (13 times the recommended human ophthalmic dose).

Teratogenicity studies with timolol in mice, rats, and rabbits at oral doses up to 50 mg/kg/day (7,000 times the systemic exposure following the maximum recommended human ophthalmic dose) demonstrated no evidence of fetal malformations. Although delayed fetal ossification was observed at this dose in rats, there were no adverse effects on postnatal development of offspring. Doses of 1000 mg/kg/day (142,000 times the systemic exposure following the maximum recommended human ophthalmic dose) were maternotoxic in mice and resulted in an increased number of fetal resorptions. Increased fetal resorptions were also seen in rabbits at doses of 14,000 times the systemic exposure following the maximum recommended human ophthalmic dose, in this case without apparent maternotoxicity.

There are no adequate and well-controlled studies in pregnant women. COSOPT should be used during pregnancy only if the potential benefit justifies the potential risk to the fetus.

Nursing Mothers

It is not known whether dorzolamide is excreted in human milk. Timolol maleate has been detected in human milk following oral and ophthalmic drug administration. Because of the potential for serious adverse reactions from COSOPT in nursing infants, a decision should be made whether to discontinue nursing or to discontinue the drug, taking into account the importance of the drug to the mother.

Pediatric Use

The safety and effectiveness of dorzolamide hydrochloride ophthalmic solution and timolol maleate ophthalmic solution have been established when administered individually in pediatric patients aged 2 years and older. Use of these drug products in these children is supported by evidence from adequate and well-controlled studies in children and adults. Safety and efficacy in pediatric patients below the age of 2 years have not been established.

Geriatric Use

No overall differences in safety or effectiveness have been observed between elderly and younger patients.

ADVERSE REACTIONS

COSOPT was evaluated for safety in 1035 patients with elevated intraocular pressure treated for open-angle glaucoma or ocular hypertension. Approximately 5% of all patients discontinued therapy with COSOPT because of adverse reactions. The most frequently reported adverse events were taste perversion (bitter, sour, or unusual taste) or ocular burning and/or stinging in up to 30% of patients. Conjunctival hyperemia, blurred vision, superficial punctate keratitis or eye itching were reported between 5-15% of patients. The following adverse events were reported in 1-5% of patients: abdominal pain, back pain, blepharitis, bronchitis, cloudy vision, conjunctival discharge, conjunctival edema, conjunctival follicles, conjunctival injection, conjunctivitis, corneal erosion, corneal staining, cortical lens opacity, cough, dizziness, dryness of eyes, dyspepsia, eye debris, eye discharge, eye pain, eye tearing, eyelid edema, eyelid erythema, eyelid exudate/scales, eyelid pain or discomfort, foreign body sensation, glaucomatous cupping, headache, hypertension, influenza, lens nucleus coloration, lens opacity, nausea, nuclear lens opacity, pharyngitis, post-subcapsular cataract, sinusitis, upper respiratory infection, urinary tract infection, visual field defect, vitreous detachment.

The following adverse events have occurred either at low incidence (<1%) during clinical trials or have been reported during the use of COSOPT in clinical practice where these events were reported voluntarily from a population of unknown size and frequency of occurrence cannot be determined precisely. They have been chosen for inclusion based on factors such as seriousness, frequency of reporting, possible causal connection to COSOPT, or a combination of these factors: bradycardia, cardiac failure, cerebral vascular accident, chest pain, choroidal detachment following filtration surgery (see PRECAUTIONS, General), depression, diarrhea, dry mouth, dyspnea, heart block, hypotension, iridocyclitis, myocardial infarction, nasal congestion, Stevens-Johnson syndrome, toxic epidermal necrolysis, paresthesia, photophobia, respiratory failure, skin rashes, urolithiasis, and vomiting.

Other adverse reactions that have been reported with the individual components are listed below:

Dorzolamide — Allergic/Hypersensitivity: Signs and symptoms of local reactions including palpebral reactions and systemic allergic reactions including angioedema, bronchospasm, pruritus, urticaria; Body as a Whole: Asthenia/fatigue; Skin/Mucous Membranes: Contact dermatitis, epistaxis, throat irritation; Special Senses: Eyelid crusting, signs and symptoms of ocular allergic reaction, and transient myopia.

Timolol (ocular administration) — Body as a Whole: Asthenia/fatigue; Cardiovascular: Arrhythmia, syncope, cerebral ischemia, worsening of angina pectoris, palpitation, cardiac arrest, pulmonary edema, edema, claudication, Raynaud’s phenomenon, and cold hands and feet; Digestive: Anorexia; Immunologic: Systemic lupus erythematosus; Nervous System/Psychiatric: Increase in signs and symptoms of myasthenia gravis, somnolence, insomnia, nightmares, behavioral changes and psychic disturbances including confusion, hallucinations, anxiety, disorientation, nervousness, and memory loss; Skin: Alopecia, psoriasiform rash or exacerbation of psoriasis; Hypersensitivity: Signs and symptoms of systemic allergic reactions, including anaphylaxis, angioedema, urticaria, and localized and generalized rash; Respiratory: Bronchospasm (predominantly in patients with pre-existing bronchospastic disease); Endocrine: Masked symptoms of hypoglycemia in diabetic patients (see WARNINGS); Special Senses: Ptosis, decreased corneal sensitivity, cystoid macular edema, visual disturbances including refractive changes and diplopia, pseudopemphigoid, and tinnitus; Urogenital: Retroperitoneal fibrosis, decreased libido, impotence, and Peyronie’s disease.

The following additional adverse effects have been reported in clinical experience with ORAL timolol maleate or other ORAL beta-blocking agents and may be considered potential effects of ophthalmic timolol maleate: Allergic: Erythematous rash, fever combined with aching and sore throat, laryngospasm with respiratory distress; Body as a Whole: Extremity pain, decreased exercise tolerance, weight loss; Cardiovascular: Worsening of arterial insufficiency, vasodilatation; Digestive: Gastrointestinal pain, hepatomegaly, mesenteric arterial thrombosis, ischemic colitis; Hematologic: Nonthrombocytopenic purpura; thrombocytopenic purpura, agranulocytosis; Endocrine: Hyperglycemia, hypoglycemia; Skin: Pruritus, skin irritation, increased pigmentation, sweating; Musculoskeletal: Arthralgia; Nervous System/Psychiatric: Vertigo, local weakness, diminished concentration, reversible mental depression progressing to catatonia, an acute reversible syndrome characterized by disorientation for time and place, emotional lability, slightly clouded sensorium, and decreased performance on neuropsychometrics; Respiratory: Rales, bronchial obstruction; Urogenital: Urination difficulties.

OVERDOSAGE

There are no human data available on overdosage with COSOPT.

Symptoms consistent with systemic administration of beta-blockers or carbonic anhydrase inhibitors may occur, including electrolyte imbalance, development of an acidotic state, dizziness, headache, shortness of breath, bradycardia, bronchospasm, cardiac arrest and possible central nervous system effects. Serum electrolyte levels (particularly potassium) and blood pH levels should be monitored (see also ADVERSE REACTIONS).

A study of patients with renal failure showed that timolol did not dialyze readily.

DOSAGE AND ADMINISTRATION

The dose is one drop of COSOPT in the affected eye(s) two times daily.

If more than one topical ophthalmic drug is being used, the drugs should be administered at least ten minutes apart (see also PRECAUTIONS, Drug Interactions).

HOW SUPPLIED

COSOPT Ophthalmic Solution is a clear, colorless to nearly colorless, slightly viscous solution.

No. 3628 — COSOPT Ophthalmic Solution is supplied in an OCUMETER® 2 PLUS container, a white, translucent, HDPE plastic ophthalmic dispenser with a controlled drop tip and a white polystyrene cap with dark blue label as follows:

NDC 54868-4279-0, 10 mL in an 18 mL capacity bottle.

2

Registered trademark of Merck Sharp & Dohme Corp., a subsidiary of Merck & Co., Inc.

Relabeling of "Additional Barcode" label by:
Physicians Total Care, Inc.
Tulsa, OK 74146

Storage

Store COSOPT at 15-30°C (59-86°F). Protect from light.

INSTRUCTIONS FOR USE

Please follow these instructions carefully when using COSOPT. Use COSOPT as prescribed by your doctor.

1. If you use other topically applied ophthalmic medications, they should be administered at least 10 minutes before or after COSOPT.
2. Wash hands before each use.
3. Before using the medication for the first time, be sure the Safety Strip on the front of the bottle is unbroken. A gap between the bottle and the cap is normal for an unopened bottle.
4. Tear off the Safety Strip to break the seal.
5. To open the bottle, unscrew the cap by turning as indicated by the arrows on the top of the cap. Do not pull the cap directly up and away from the bottle. Pulling the cap directly up will prevent your dispenser from operating properly.
6. Tilt your head back and pull your lower eyelid down slightly to form a pocket between your eyelid and your eye.
7. Invert the bottle, and press lightly with the thumb or index finger over the “Finger Push Area” (as shown) until a single drop is dispensed into the eye as directed by your doctor.
  DO NOT TOUCH YOUR EYE OR EYELID WITH THE DROPPER TIP.
  OPHTHALMIC MEDICATIONS, IF HANDLED IMPROPERLY, CAN BECOME CONTAMINATED BY COMMON BACTERIA KNOWN TO CAUSE EYE INFECTIONS. SERIOUS DAMAGE TO THE EYE AND SUBSEQUENT LOSS OF VISION MAY RESULT FROM USING CONTAMINATED OPHTHALMIC MEDICATIONS. IF YOU THINK YOUR MEDICATION MAY BE CONTAMINATED, OR IF YOU DEVELOP AN EYE INFECTION, CONTACT YOUR DOCTOR IMMEDIATELY CONCERNING CONTINUED USE OF THIS BOTTLE.
8. If drop dispensing is difficult after opening for the first time, replace the cap on the bottle and tighten (DO NOT OVERTIGHTEN) and then remove by turning the cap in the opposite direction as indicated by the arrows on the top of the cap.
9. Repeat steps 6 & 7 with the other eye if instructed to do so by your doctor.
10. Replace the cap by turning until it is firmly touching the bottle. The arrow on the left side of the cap must be aligned with the arrow on the left side of the bottle label for proper closure. Do not overtighten or you may damage the bottle and cap.
11. The dispenser tip is designed to provide a single drop; therefore, do NOT enlarge the hole of the dispenser tip.
12. After you have used all doses, there will be some COSOPT left in the bottle. You should not be concerned since an extra amount of COSOPT has been added and you will get the full amount of COSOPT that your doctor prescribed. Do not attempt to remove excess medicine from the bottle.

WARNING: Keep out of reach of children.

If you have any questions about the use of COSOPT, please consult your doctor.

Manuf. for: Merck Sharp & Dohme Corp., a subsidiary of
MERCK & CO., INC., Whitehouse Station, NJ 08889, USA

By: Laboratories Merck Sharp & Dohme-Chibret
63963 Clermont-Ferrand Cedex 9, France

Issued December 2009

9711305

219A-12/09 516149Z

PATIENT PACKAGE INSERT

Patient Information about
COSOPT® (dorzolamide hydrochloride–timolol maleate ophthalmic solution)
COSOPT (pronounced “CO-sopt”)

Read this information before you start using COSOPT and each time you refill your prescription. This is in case any information has changed. This leaflet provides a summary of certain information about COSOPT. Your doctor or pharmacist can give you more complete information about COSOPT. This leaflet does not take the place of careful discussions with your doctor. You and your doctor should discuss COSOPT when you start using your medicine and at regular checkups. Only your doctor can prescribe COSOPT for you.

What is COSOPT?

COSOPT is an eyedrop. It contains dorzolamide hydrochloride, which is an ophthalmic carbonic anhydrase inhibiting drug. It also contains timolol maleate, which is a beta-blocking drug. Both drugs work to lower pressure in the eye, but in different ways.

COSOPT is a medicine for lowering pressure in the eye in people with open-angle glaucoma or ocular hypertension. It is used when a beta-blocker eyedrop alone is not adequate to control eye pressure.

What should I know about high pressure in the eye?

People with open-angle glaucoma or ocular hypertension have pressures in one or both of their eye(s) that are too high for them.

High pressure in the eye may damage the optic nerve. This may lead to loss of vision and possible blindness. There generally are few symptoms that you can feel to tell you whether you have high pressure within your eye. Your doctor needs to examine your eyes to determine this. If you have high pressure in your eye, you will need your pressure checked and your eyes examined regularly.

Who should not use COSOPT?

Do not use COSOPT if you have:

- asthma or have ever had asthma,
- severe lung problems,
- slow or irregular heartbeat or heart failure,
- allergies to any of its ingredients. See the list at the end of the leaflet.

If you are not sure whether you should use COSOPT, contact your doctor or pharmacist.

What should I tell my doctor before and during treatment with COSOPT?

Tell your doctor:

- if you are pregnant or plan to become pregnant,
- if you are breast-feeding or intend to breast-feed,
- about any medical problems you have now or had in the past, especially heart problems or breathing problems including asthma,
- if you now have or had in the past kidney or liver problems,
- if you have diabetes, thyroid disease or muscle weakness,
- about all medicines that you are taking or plan to take, including those you can get without a prescription,
- about any allergies including allergies to any medications, especially sulfa drugs,
- if you develop an eye infection, develop a red or swollen eye or eyelid, receive an eye injury, have eye surgery, or develop new or worsening eye symptoms,
- if you plan on having any type of surgery.

How should I use COSOPT?

COSOPT is an eyedrop. The usual dose is one drop in the morning and one drop in the evening. Your doctor will tell you if just one or both eyes are to be treated.

If you are using COSOPT with another eyedrop, the eyedrops should be used at least 10 minutes apart. It is very important to use your medication exactly as directed by your doctor. If you stop using your medicine, contact your doctor immediately.

COSOPT contains a preservative called benzalkonium chloride. This preservative may be absorbed by soft contact lenses. Contact lenses should be removed before using COSOPT. The lenses can be placed back into your eyes 15 minutes after using the eyedrops.

Do not allow the tip of the bottle to touch the eye or areas around the eye. The bottle may become contaminated with bacteria. This can cause eye infections leading to serious damage to the eye, even loss of vision. Keep the tip of the bottle away from contact with any surface to avoid contamination.

INSTRUCTIONS FOR USE

Please follow these instructions carefully when using COSOPT. Use COSOPT as prescribed by your doctor.

1. If you use other topically applied ophthalmic medications, they should be administered at least 10 minutes before or after COSOPT.
2. Wash hands before each use.
3. Before using the medication for the first time, be sure the Safety Strip on the front of the bottle is unbroken. A gap between the bottle and the cap is normal for an unopened bottle.
4. Tear off the Safety Strip to break the seal.
5. To open the bottle, unscrew the cap by turning as indicated by the arrows on the top of the cap. Do not pull the cap directly up and away from the bottle. Pulling the cap directly up will prevent your dispenser from operating properly.
6. Tilt your head back and pull your lower eyelid down slightly to form a pocket between your eyelid and your eye.
7. Invert the bottle, and press lightly with the thumb or index finger over the “Finger Push Area” (as shown) until a single drop is dispensed into the eye as directed by your doctor.
  DO NOT TOUCH YOUR EYE OR EYELID WITH THE DROPPER TIP.
  OPHTHALMIC MEDICATIONS, IF HANDLED IMPROPERLY, CAN BECOME CONTAMINATED BY COMMON BACTERIA KNOWN TO CAUSE EYE INFECTIONS. SERIOUS DAMAGE TO THE EYE AND SUBSEQUENT LOSS OF VISION MAY RESULT FROM USING CONTAMINATED OPHTHALMIC MEDICATIONS. IF YOU THINK YOUR MEDICATION MAY BE CONTAMINATED, OR IF YOU DEVELOP AN EYE INFECTION, CONTACT YOUR DOCTOR IMMEDIATELY CONCERNING CONTINUED USE OF THIS BOTTLE.
8. If drop dispensing is difficult after opening for the first time, replace the cap on the bottle and tighten (DO NOT OVERTIGHTEN) and then remove by turning the cap in the opposite direction as indicated by the arrows on the top of the cap.
9. Repeat steps 6 & 7 with the other eye if instructed to do so by your doctor.
10. Replace the cap by turning until it is firmly touching the bottle. The arrow on the left side of the cap must be aligned with the arrow on the left side of the bottle label for proper closure. Do not overtighten or you may damage the bottle and cap.
11. The dispenser tip is designed to provide a single drop; therefore, do NOT enlarge the hole of the dispenser tip.
12. After you have used all doses, there will be some COSOPT left in the bottle. You should not be concerned since an extra amount of COSOPT has been added and you will get the full amount of COSOPT that your doctor prescribed. Do not attempt to remove excess medicine from the bottle.

Can I use COSOPT with other medicines?

Tell your doctor or pharmacist about all drugs that you are using or plan to use. This includes other eyedrops and drugs obtained without a prescription. This is particularly important if you are taking medicine to lower blood pressure or to treat heart disease, or if you are taking large doses of aspirin.

Ask your doctor’s advice about taking COSOPT if you are also using:

- oral carbonic anhydrase inhibitors (for example, acetazolamide, Diamox®)
- oral beta-blockers (for example, propranolol, Inderal®)
- calcium antagonists (for example, nifedipine, Procardia®)
- catecholamine-depleting drugs (for example, reserpine)
- digitalis in combination with calcium antagonists (for example, Lanoxin® with Procardia®)
- quinidine (for example, Cardioquin®)
- clonidine (for example, Catapres®)
- injectable epinephrine (for example, EpiPen®)
- SSRIs (for example, Prozac®)

Your doctor or pharmacist can tell you if any of the drugs you are using are in the above list.

What are the possible side effects of COSOPT?

Any medicine may have unintended or undesirable effects. These are called side effects. Side effects may not occur, but if they do occur, you may need medical attention. The most common side effects you may experience are:

- eye symptoms such as burning and stinging, redness of the eye(s), blurred vision, tearing or itching.
- a bitter, sour or unusual taste after putting in your eyedrops.

Other side effects may occur rarely, and some of these may be serious. Tell your doctor right away if you experience:

- shortness of breath
- visual changes
- an irregular heartbeat and/or a slowing of your heart rate
- severe skin reactions

The above list is NOT a complete list of side effects reported with COSOPT. Your doctor can discuss with you a more complete list of side effects. Please tell your doctor [or pharmacist] promptly about any of these or any other unusual symptom.

What should I do in case of an overdose?

If you swallow the contents of the bottle, contact your doctor immediately. Among other effects, you may feel light-headed, have difficulty breathing, or feel your heart rate has slowed.

How should I store COSOPT?

Keep your medicine in a safe place where children cannot reach it. Store COSOPT at room temperature (59-86°F, 15-30°C). Protect the bottle from light. Do not use your medicine after the expiration date on the bottle.

What else should I know about COSOPT?

Do not use COSOPT for a condition for which it was not prescribed. Do not give COSOPT to other people, even if they have the same condition you have. It may harm them.

Inactive ingredients:

The inactive ingredients of COSOPT are sodium citrate, hydroxyethylcellulose, sodium hydroxide, mannitol, water for injection and benzalkonium chloride added as a preservative.

Merck Sharp & Dohme Corp., a subsidiary of Merck & Co., Inc.
Whitehouse Station, NJ 08889, USA

Issued December 2009

9711305

219A-12/09 516149Z

This is a representative sample of the packaging. Please see How Supplied section for a complete list of available packaging. PRINCIPAL DISPLAY PANEL - Carton 10 mL

PRINCIPAL DISPLAY PANEL

10 mL OCUMETER® PLUS
OPHTHALMIC DISPENSER
STERILE OPHTHALMIC SOLUTION

COSOPT®
(DORZOLAMIDE HYDROCHLORIDE-TIMOLOL MALEATE OPHTHALMIC SOLUTION)

(Dorzolamide Hydrochloride 22.3 mg/mL
Timolol Maleate 6.8 mg/mL)

Rx only